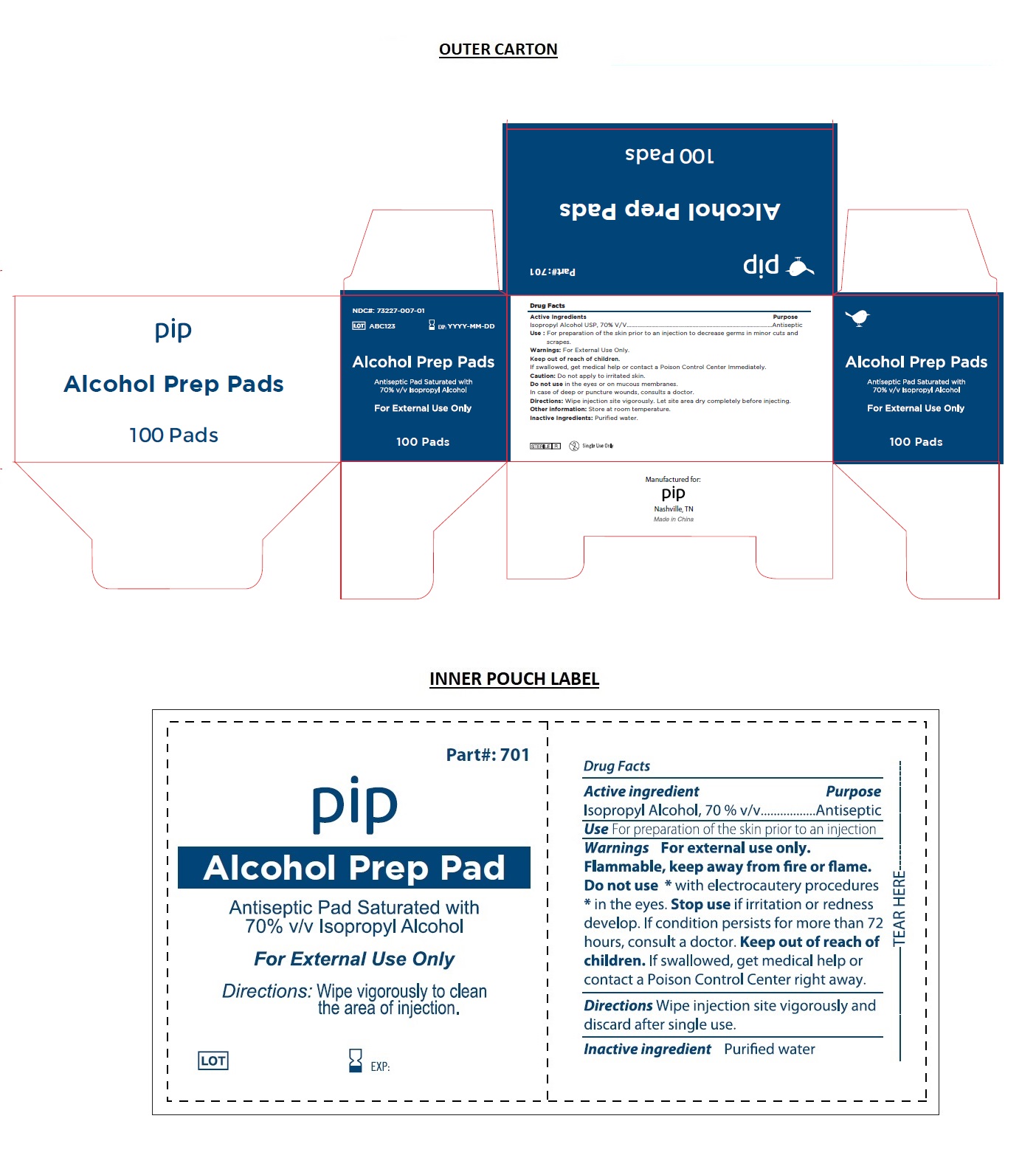 DRUG LABEL: pip
NDC: 73227-007 | Form: SWAB
Manufacturer: Amity Holdings, LLC dba Medicore Medical Supply
Category: otc | Type: HUMAN OTC DRUG LABEL
Date: 20190712

ACTIVE INGREDIENTS: ISOPROPYL ALCOHOL 70 mL/100 mL
INACTIVE INGREDIENTS: WATER

pip- Alcohol Prep Pads

Active Ingredient

Isopropyl Alcohol USP, 70% V/V

Purpose

Antiseptic

Use:

For preparation of the skin prior to an injection to decrease germs in minor cuts and scrapes.

Warnings:

For external use only.

Flammable, keep away from fire or flame.

Caution: Do not apply to irritated skin.

Do not use * with electrocautery procedures

Do not use in the eyes or on mucous membranes.

In case of deep or puncture wounds, consults a doctor.

Stop use if irritation or redness develop. If condition persists for more than 72 hours, consult a doctor.

Keep out of reach of children.

If swallowed, get medical help or contact a Poison Control Center Immediately.

Directions:

Wipe injection site vigorously and discard after single use. Let site area dry completely before injecting.

Other information:

Store at room temperature.

Inactive Ingredients:

Puriﬁed water.

Antiseptic Pad Saturated with 70% v/v Isopropyl Alcohol

Single Use Only